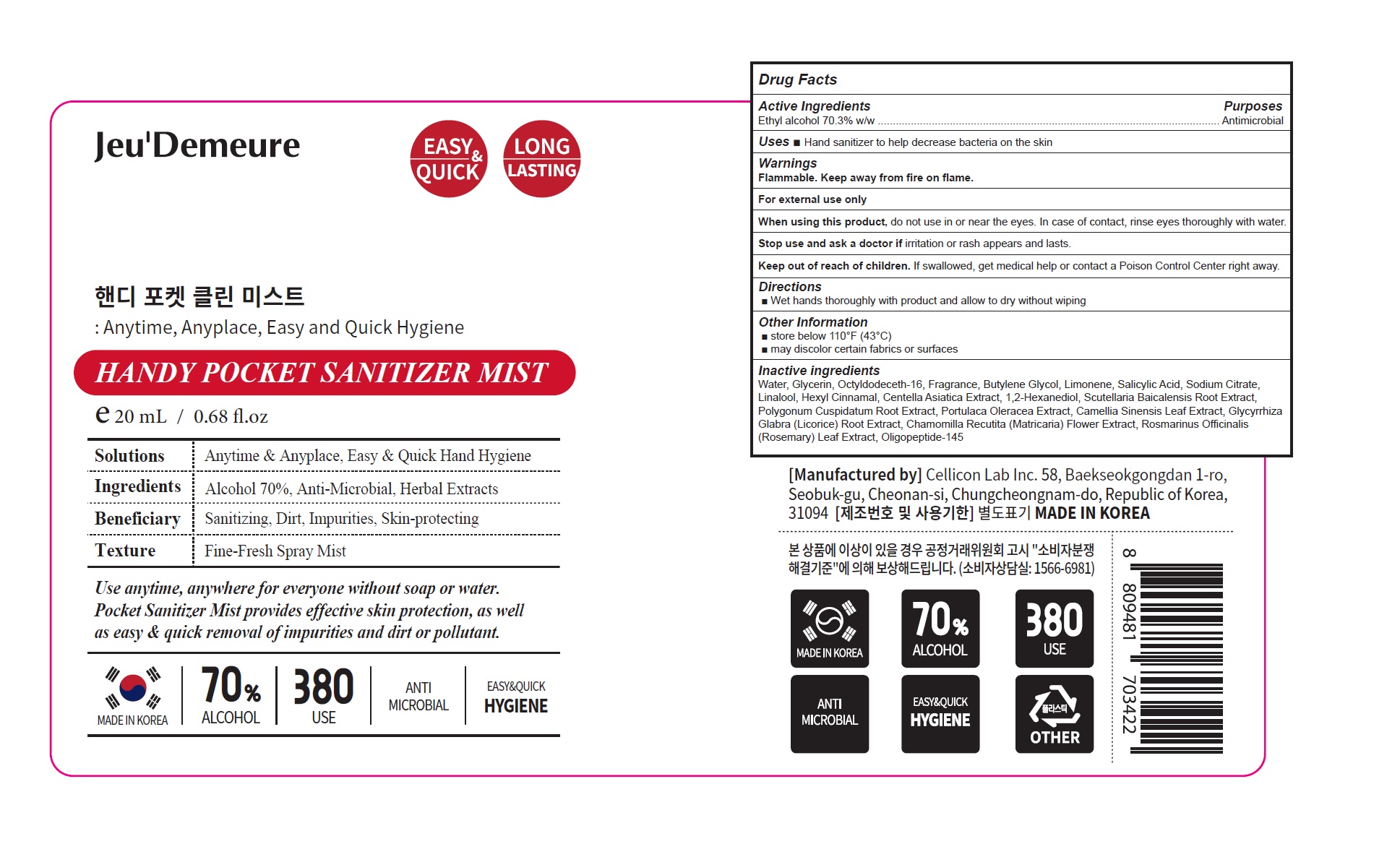 DRUG LABEL: HANDY POCKET SANITIZER MIST
NDC: 81601-003 | Form: SPRAY
Manufacturer: Cellicon Lab Inc.
Category: otc | Type: HUMAN OTC DRUG LABEL
Date: 20210402

ACTIVE INGREDIENTS: ALCOHOL 0.703 mL/1 mL
INACTIVE INGREDIENTS: WATER; GLYCERIN; OCTYLDODECETH-16; BUTYLENE GLYCOL; LIMONENE, (+)-; SALICYLIC ACID; SODIUM CITRATE, UNSPECIFIED FORM; LINALOOL, (+/-)-; .ALPHA.-HEXYLCINNAMALDEHYDE; CENTELLA ASIATICA WHOLE; 1,2-HEXANEDIOL; SCUTELLARIA BAICALENSIS ROOT; REYNOUTRIA JAPONICA ROOT; PURSLANE; GREEN TEA LEAF; GLYCYRRHIZA GLABRA; CHAMOMILE; ROSEMARY

81601-003_HANDY POCKET SANITIZER MIST

Active ingredient

Ethyl alcohol 70.3% w/w

Purpose

Antimicrobial

Use

- Hand sanitizer to help decrease bacteria on the skin

Warnings

Flammable. Keep away from fire or flame.

For external use only

When using this product do not use in or near the eyes. In case of contact, rinse eyes thoroughly with water.

Stop use and ask a doctor if irritation or rash appears and lasts

Keep out of reach of children.

Other information

- Store below 110°F (43°C)
- May discolor certain fabrics or surfaces

Directions

Wet hands thoroughly with product and allow to dry without wiping

Inactive ingredients

Water, Glycerin, Octyldodeceth-16, Fragrance, Butylene Glycol, Limonene, Salicylic Acid, Sodium Citrate, Linalool, Hexyl Cinnamal, Centella Asiatica Extract, 1,2-Hexanediol, Scutellaria Baicalensis Root Extract, Polygonum Cuspidatum Root Extract, Portulaca Oleracea Extract, Camellia Sinensis Leaf Extract, Glycyrrhiza Glabra (Licorice) Root Extract, Chamomilla Recutita (Matricaria) Flower Extract, Rosmarinus Officinalis (Rosemary) Leaf Extract, Oligopeptide-145